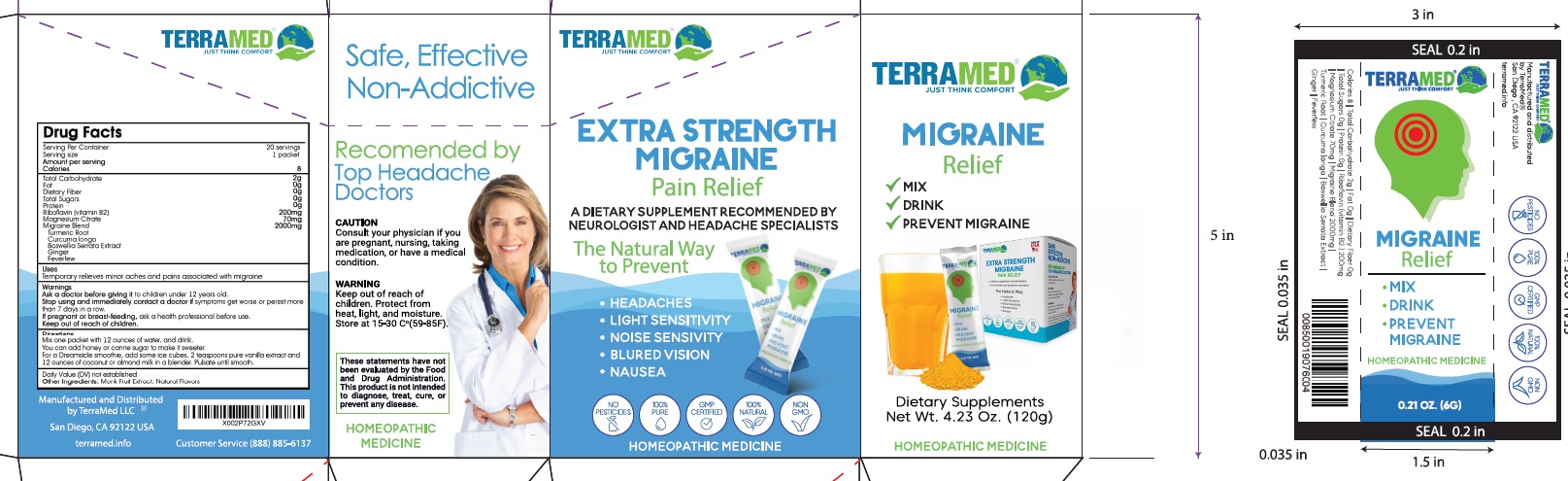 DRUG LABEL: Migraine Relief
NDC: 83004-003 | Form: POWDER
Manufacturer: Rida LLC
Category: otc | Type: HUMAN OTC DRUG LABEL
Date: 20250307

ACTIVE INGREDIENTS: TURMERIC 2 [hp_X]/6 g; CURCUMA AROMATICA ROOT 4 [hp_X]/6 g; INDIAN FRANKINCENSE 4 [hp_X]/6 g; GINGER 5 [hp_X]/6 g; FEVERFEW 3 [hp_X]/6 g
INACTIVE INGREDIENTS: RIBOFLAVIN; MAGNESIUM; SIRAITIA GROSVENORII FRUIT

Drug Facts

Active Ingredient

Turmeric Root 2X HPUS
Curcuma longa 4X HPUS
Boswelia Serrata Extract 4X HPUS
Ginger 5X HPUS
Feverflew 3X HPUS

Purpose

Temporarily relieves acute symptoms of migraine headaches such as: pressure, pulsating, stabbing headache, nausea, sensitivity

Uses

Temporarily relieves acute symptoms of migraine headaches such as: pressure, pulsating, stabbing headache, nausea, sensitivity

Warnings

Ask a doctor before giving it to children under 12 years old.

Stop using immediately contact a doctor if symptoms get worse or persist more than 7 days in a row.

If pregnant or breast-feeding, ask a health professional before use.

Keep out of reach of children

Directions

Mix one packet with 12 ounces of water, one drink.

You can add honey or cane sugar to make it sweeter.

For a Dreamsicle smoothie, add some ice cubes, 2 teaspoons pure vanilla extract and 12 ounces of coconut and almond milk in a blender. Pulsate until smooth

Inactive Ingredients

RIBOFLAVIN, MAGNESIUM, SIRAITIA GROSVENORII FRUIT